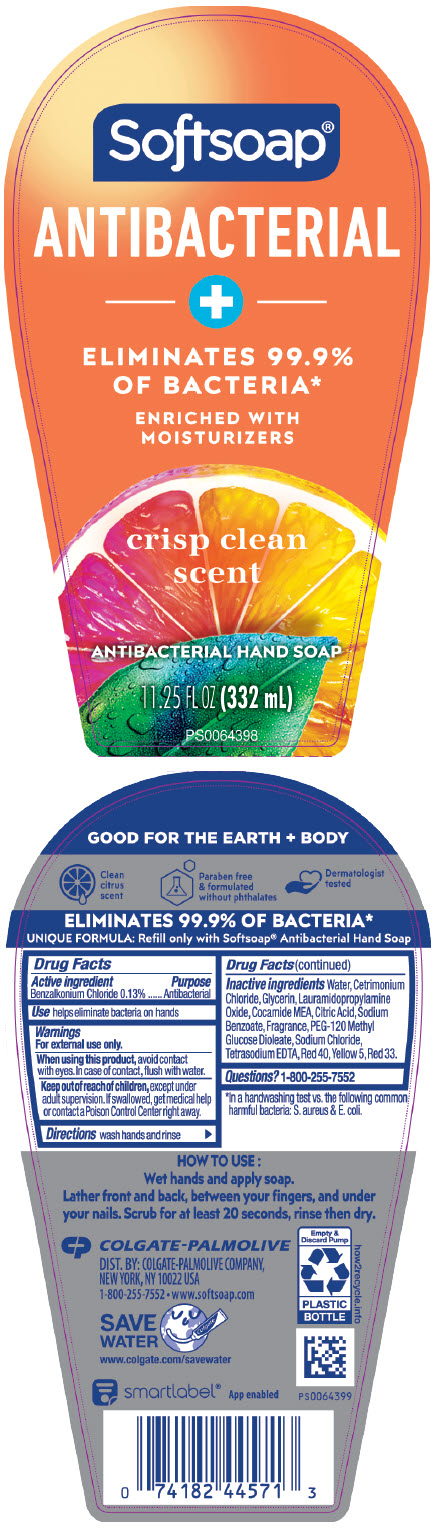 DRUG LABEL: Softsoap Antibacterial with Moisturizers Crisp Clean LHS
NDC: 35000-251 | Form: LIQUID
Manufacturer: Colgate-Palmolive Company
Category: otc | Type: HUMAN OTC DRUG LABEL
Date: 20241213

ACTIVE INGREDIENTS: BENZALKONIUM CHLORIDE 1.33 mg/1 mL
INACTIVE INGREDIENTS: WATER; CETRIMONIUM CHLORIDE; GLYCERIN; LAURAMIDOPROPYLAMINE OXIDE; COCO MONOETHANOLAMIDE; ANHYDROUS CITRIC ACID; SODIUM BENZOATE; PEG-120 METHYL GLUCOSE DIOLEATE; SODIUM CHLORIDE; EDETATE SODIUM; FD&C RED NO. 40; FD&C YELLOW NO. 5; D&C RED NO. 33

Softsoap Antibacterial with Moisturizers Crisp Clean LHS

Drug Facts

Active ingredient

Benzalkonium Chloride 0.13%

Purpose

Antibacterial

Use

helps eliminate bacteria on hands

Warnings

For external use only.

When using this product, avoid contact with eyes.

In case of contact, flush with water.

Keep out of reach of children, except under adult supervision. If swallowed, get medical help or contact a Poison Control Center right away.

Directions

wash hands and rinse

Inactive ingredients

Water, Cetrimonium Chloride, Glycerin, Lauramidopropylamine Oxide, Cocamide MEA, Citric Acid, Sodium Benzoate, Fragrance, PEG-120 Methyl Glucose Dioleate, Sodium Chloride, Tetrasodium EDTA, Red 40, Yellow 5, Red 33.

Questions?

1-800-255-7552

DIST. BY:
COLGATE-PALMOLIVE COMPANY, NEW YORK, NY 10022 USA

PRINCIPAL DISPLAY PANEL - 332 mL Bottle Label

Softsoap®

ANTIBACTERIAL

+

ELIMINATES 99.9%
OF BACTERIA*

ENRICHED WITH
MOISTURIZERS

crisp clean
scent

ANTIBACTERIAL HAND SOAP

11.25 FL OZ (332 mL)

PS0064398